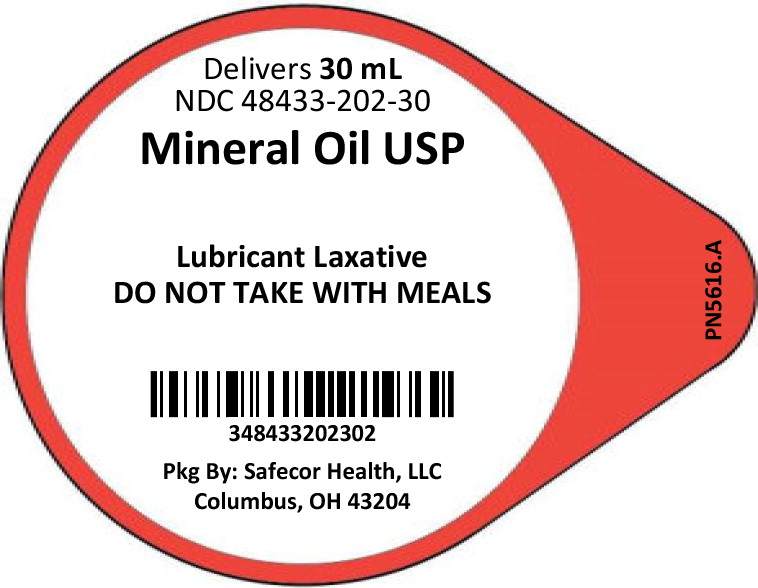 DRUG LABEL: Mineral Oil
NDC: 48433-202 | Form: SOLUTION
Manufacturer: Safecor Health, LLC
Category: otc | Type: HUMAN OTC DRUG LABEL
Date: 20250108

ACTIVE INGREDIENTS: MINERAL OIL 1000 mg/1 mL
INACTIVE INGREDIENTS: .ALPHA.-TOCOPHEROL

SAFECOR HEALTH
Mineral Oil USP 30 mL Unit Dose
Drug Facts

Active Ingredients

Mineral Oil USP

Purpose

Lubricant Laxative

Use:

For relief of occasional constipation (irregularity). Generally produces bowel movements in 6 to 8 hours

WARNINGS:

Do not use * if you have difficulty swallowing * in children under 6 years of age * if you are pregnant * for a period longer than 1 week * if you are bedridden or aged.

Ask a doctor before use if you have *abdominal pain, nausea, or vomiting *noticed a sudden change in bowel habits that persist over a period of 2 weeks.

Ask a Doctor or Pharmacist before use if you are: * presently taking a stool softener * taking any other drug. Take this product 2 or more hours before or after drugs. Laxatives may affect how other drugs work. Frequent or prolonged use may result in dependence.

When using this product: Do not take with meals. Take only at bedtime.

Stop use and ask a doctor if you have rectal bleeding or failure to have a bowel movement after use. These could be signs of a serious condition.

PREGNANCY OR BREAST FEEDING

If breast feeding, ask a health care professional before use.

KEEP OUT OF REACH OF CHILDREN

Keep this and all drugs out of reach of children. In case of overdose, get medical help or contact a Poison Control Center right away. In case of eye contact, flush with water.

DOSAGE AND ADMINISTRATION

Directions: * Do not take with meals. Take only at bedtime. May be taken as a single daily dose or in divided doses.
Adults and children 12 years of age and over | 1 to 3 Tablespoons (15 mL to 45 mL), maximum 3 Tablespoons (45 mL) in 24 hours
Children 6 to under 12 years of age | 1 to 3 teaspoons (5 mL to 15 mL), maximum 3 teaspoons (15 mL) in 24 hours
Children under 6 years | Do not use. Consult a doctor

Other information: Keep tightly closed. Protect from sunlight. For more info call 800-447-1006.

Inactive ingredients: Mixed tocopherols (added as a stabilizer)

NDC: 48433-202-30 Mineral Oil USP 30 mL Unit Dose Cup

Mfd. in the U.S.A.
Distributed by: Safecor Health, LLC
4060 Business Park Drive, Columbus, OH 43204
Rev: 05/2019 PN5471

Principal Display Panel - Lid Label

Delivers 30 mL

NDC 48433-202-30

Mineral Oil USP

Lubricant Laxative

DO NOT TAKE WITH MEALS

348433202302

Pkg By: Safecor Health, LLC

Columbus, OH 43204